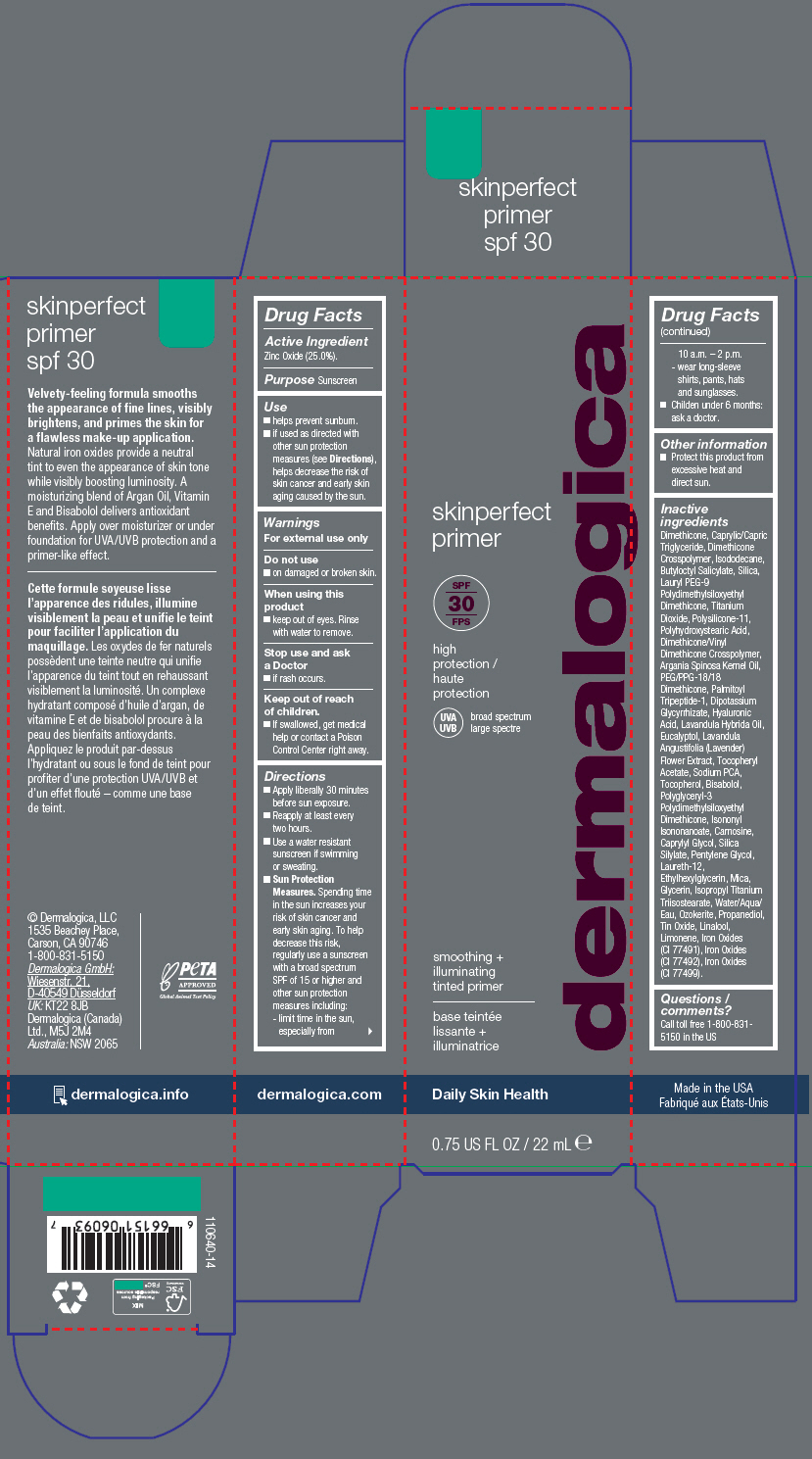 DRUG LABEL: SKINPERFECT PRIMER SPF30
NDC: 68479-132 | Form: LOTION
Manufacturer: Dermalogica, LLC.
Category: otc | Type: HUMAN OTC DRUG LABEL
Date: 20240423

ACTIVE INGREDIENTS: Zinc Oxide 24.96 mg/100 mL
INACTIVE INGREDIENTS: Dimethicone; MEDIUM-CHAIN TRIGLYCERIDES; Isododecane; Butyloctyl Salicylate; SILICON DIOXIDE; Lauryl PEG-9 Polydimethylsiloxyethyl Dimethicone; DIMETHICONE/VINYL DIMETHICONE CROSSPOLYMER (SOFT PARTICLE); POLYHYDROXYSTEARIC ACID (2300 MW); DIMETHICONE/VINYL DIMETHICONE CROSSPOLYMER (HARD PARTICLE); Titanium Dioxide; ARGAN OIL; PEG/PPG-18/18 Dimethicone; Water; FERRIC OXIDE RED; FERRIC OXIDE YELLOW; FERROSOFERRIC OXIDE; POLYGLYCERYL-3 POLYDIMETHYLSILOXYETHYL DIMETHICONE (4000 MPA.S); Mica; Isononyl Isononanoate; .ALPHA.-TOCOPHEROL ACETATE; LAVANDIN OIL; LEVOMENOL; CERESIN; Pentylene Glycol; Propanediol; Carnosine; GLYCYRRHIZINATE DIPOTASSIUM; Caprylyl Glycol; Glycerin; Isopropyl Titanium Triisostearate; Ethylhexylglycerin; SODIUM PIDOLATE; Laureth-12; Hyaluronic Acid; Eucalyptol; STANNIC OXIDE; LAVANDULA ANGUSTIFOLIA SUBSP. ANGUSTIFOLIA FLOWER; Tocopherol; Palmitoyl Tripeptide-1

SKINPERFECT PRIMER SPF30

Drug Facts

Active Ingredient

Zinc Oxide (25.0%).

Purpose

Sunscreen

Use

- helps prevent sunburn.
- if used as directed with other sun protection measures (see Directions), helps decrease the risk of skin cancer and early skin aging caused by the sun.

Warnings

For external use only

Do not use

- on damaged or broken skin.

When using this product

- keep out of eyes. Rinse with water to remove.

Stop use and ask a Doctor

- if rash occurs.

Keep out of reach of children.

- If swallowed, get medical help or contact a Poison Control Center right away.

Directions

- Apply liberally 30 minutes before sun exposure.
- Reapply at least every two hours.
- Use a water resistant sunscreen if swimming or sweating.
- Sun Protection Measures. Spending time in the sun increases your risk of skin cancer and early skin aging. To help decrease this risk, regularly use a sunscreen with a broad spectrum SPF of 15 or higher and other sun protection measures including:
  - limit time in the sun, especially from 10 a.m. – 2 p.m.
  - wear long-sleeve shirts, pants, hats and sunglasses.
- Childen under 6 months: ask a doctor.

Other information

- Protect this product from excessive heat and direct sun.

Inactive ingredients

Dimethicone, Caprylic/Capric Triglyceride, Dimethicone Crosspolymer, Isododecane, Butyloctyl Salicylate, Silica, Lauryl PEG-9 Polydimethylsiloxyethyl Dimethicone, Titanium Dioxide, Polysilicone-11, Polyhydroxystearic Acid, Dimethicone/Vinyl Dimethicone Crosspolymer, Argania Spinosa Kernel Oil, PEG/PPG-18/18 Dimethicone, Palmitoyl Tripeptide-1, Dipotassium Glycyrrhizate, Hyaluronic Acid, Lavandula Hybrida Oil, Eucalyptol, Lavandula Angustifolia (Lavender) Flower Extract, Tocopheryl Acetate, Sodium PCA, Tocopherol, Bisabolol, Polyglyceryl-3 Polydimethylsiloxyethyl Dimethicone, Isononyl Isononanoate, Carnosine, Caprylyl Glycol, Silica Silylate, Pentylene Glycol, Laureth-12, Ethylhexylglycerin, Mica, Glycerin, Isopropyl Titanium Triisostearate, Water/Aqua/Eau, Ozokerite, Propanediol, Tin Oxide, Linalool, Limonene, Iron Oxides (CI 77491), Iron Oxides (CI 77492), Iron Oxides (CI 77499).

Questions / comments?

Call toll free 1-800-831-5150 in the US

PRINCIPAL DISPLAY PANEL - 22 mL Tube Carton

skinperfect
primer

SPF
30

high
protection

UVA
UVB
broad spectrum

smoothing +
illuminating
tinted primer

Daily Skin Health

0.75 US FL OZ / 22 mL ℮

dermalogica